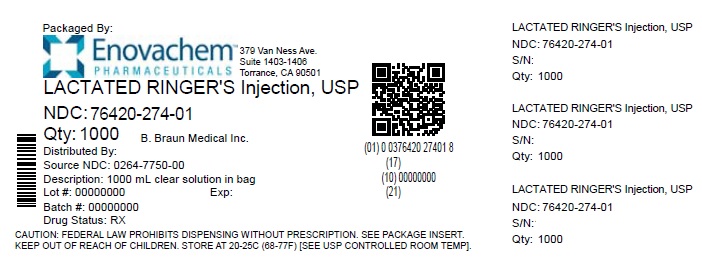 DRUG LABEL: Lactated Ringers
NDC: 76420-274 | Form: INJECTION, SOLUTION
Manufacturer: Asclemed USA, Inc.
Category: prescription | Type: HUMAN PRESCRIPTION DRUG LABEL
Date: 20240507

ACTIVE INGREDIENTS: SODIUM CHLORIDE 0.6 g/100 mL; SODIUM LACTATE 0.31 g/100 mL; POTASSIUM CHLORIDE 0.03 g/100 mL; CALCIUM CHLORIDE 0.02 g/100 mL
INACTIVE INGREDIENTS: WATER

Lactated Ringer's Injection USP

DESCRIPTION

Rx only

Each 100 mL of Lactated Ringer's Injection USP contains:
Sodium Chloride USP 0.6 g; Sodium Lactate 0.31 g
Potassium Chloride USP 0.03 g; Calcium Chloride Dihydrate USP 0.02 g
Water for Injection USP qs

pH may be adjusted with Hydrochloric Acid NF or Sodium Hydroxide NF
pH: 6.2 (6.0–7.5) Calculated Osmolarity: 275 mOsmol/liter

Concentration of Electrolytes (mEq/liter): Sodium 130; Potassium 4;
Calcium 3; Chloride 110; Lactate (CH3CH(OH)COO^−) 28

Lactated Ringer's Injection USP is sterile, nonpyrogenic and contains no bacteriostatic or antimicrobial agents. This product is intended for intravenous administration in a single dose container.

The formulas of the active ingredients are:

Ingredients | Molecular Formula | Molecular Weight
Sodium Chloride USP | NaCl | 58.44
Sodium Lactate | CH3CH(OH)COONa | 112.06
Potassium Chloride USP | KCl | 74.55
Calcium Chloride Dihydrate USP | CaCl2•2H2O | 147.02

Not made with natural rubber latex, PVC or DEHP.

The plastic container is made from a multilayered film specifically developed for parenteral drugs. It contains no plasticizers and exhibits virtually no leachables. The solution contact layer is a rubberized copolymer of ethylene and propylene. The container is nontoxic and biologically inert. The container-solution unit is a closed system and is not dependent upon entry of external air during administration. The container is overwrapped to provide protection from the physical environment and to provide an additional moisture barrier when necessary.

Addition of medication should be accomplished using complete aseptic technique.

The closure system has two ports; the one for the administration set has a tamper evident plastic protector and the other is a medication addition site. Refer to the Directions for Use of the container.

CLINICAL PHARMACOLOGY

Lactated Ringer's Injection USP provides electrolytes and is a source of water for hydration. It is capable of inducing diuresis depending on the clinical condition of the patient. This solution also contains lactate which produces a metabolic alkalinizing effect.

Sodium, the major cation of the extracellular fluid, functions primarily in the control of water distribution, fluid balance, and osmotic pressure of body fluids. Sodium is also associated with chloride and bicarbonate in the regulation of the acid-base equilibrium of body fluid. Potassium, the principal cation of intracellular fluid, participates in carbohydrate utilization and protein synthesis, and is critical in the regulation of nerve conduction and muscle contraction, particularly in the heart.

Chloride, the major extracellular anion, closely follows the metabolism of sodium, and changes in the acid-base balance of the body are reflected by changes in the chloride concentration. Calcium, an important cation, provides the framework of bones and teeth in the form of calcium phosphate and calcium carbonate. In the ionized form, calcium is essential for the functional mechanism of the clotting of blood, normal cardiac function, and regulation of neuromuscular irritability.

Sodium lactate is a racemic salt containing both the levo form, which is oxidized by the liver to bicarbonate, and the dextro form, which is converted to glycogen. Lactate is slowly metabolized to carbon dioxide and water, accepting one hydrogen ion and resulting in the formation of bicarbonate for the lactate consumed. These reactions depend on oxidative cellular activity.

INDICATIONS AND USAGE

This solution is indicated for use in adults and pediatric patients as a source of electrolytes and water for hydration.

CONTRAINDICATIONS

The use of Lactated Ringer’s Injection USP is contraindicated in neonates (28 days of age or younger) receiving concomitant treatment with ceftriaxone, even if separate infusion lines are used, due to the risk of fatal ceftriaxone-calcium salt precipitation in the neonate’s bloodstream [see Warnings, Drug Interactions, Pediatric Use].

This solution is contraindicated where the administration of sodium, potassium, calcium, lactate, or chloride could be clinically detrimental.

Lactate administration is contraindicated in severe metabolic acidosis or alkalosis, and in severe liver disease or anoxic states which affect lactate metabolism.

WARNINGS

Precipitation with Ceftriaxone

Precipitation of ceftriaxone-calcium can occur when ceftriaxone is mixed with calcium-containing solutions, such as Lactated Ringer’s Injection USP, in the same intravenous administration line. Do not administer ceftriaxone simultaneously with Lactated Ringer’s Injection USP via a Y-site.

Deaths have occurred in neonates (28 days of age or younger) who received concomitant intravenous calcium-containing solutions with ceftriaxone resulting from calcium-ceftriaxone precipitates in the lungs and kidneys, even when separate infusion lines were used. Lactated Ringer’s Injection USP is contraindicated in neonates receiving ceftriaxone.

However, in patients other than neonates, ceftriaxone and Lactated Ringer’s Injection USP may be administered sequentially if the infusion lines are thoroughly flushed between infusions with a compatible fluid. [see Contraindications, Warnings, Drug Interactions, Pediatric Use].

Solutions containing lactate are not for use in the treatment of lactic acidosis.

Solutions containing lactate should be used with great care in patients with metabolic or respiratory alkalosis, and in those conditions in which there is an increased level or an impaired utilization of lactate, such as severe hepatic insufficiency.

The administration of intravenous solutions can cause fluid and/or solute overload resulting in dilution of serum electrolyte concentrations, overhydration, congested states or pulmonary edema. The risk of dilutional states is inversely proportional to the electrolyte concentration. The risk of solute overload causing congested states with peripheral and pulmonary edema is directly proportional to the electrolyte concentration.

Solutions containing sodium ions should be used with great care, if at all, in patients with congestive heart failure, severe renal insufficiency, and in clinical states in which there is sodium retention with edema.

Solutions containing potassium ions should be used with great care, if at all, in patients with hyperkalemia, severe renal failure, and in conditions in which potassium ions retention is present.

In patients with diminished renal function, administration of solutions containing sodium or potassium ions may result in sodium or potassium retention.

Solutions containing calcium ions should not be administered through the same administration set as blood because of the likelihood of coagulation.

PRECAUTIONS

General

This solution should be used with care in patients with hypervolemia, renal insufficiency, urinary tract obstruction, or impending or frank cardiac decompensation.

Extraordinary electrolytes losses such as may occur during protracted nasogastric suction, vomiting, diarrhea or gastrointestinal fistula drainage may necessitate additional electrolyte supplementation.

Additional essential electrolytes, minerals and vitamins should be supplied as needed.

Sodium-containing solutions should be administered with caution to patients receiving corticosteroids or corticotropin, or to other salt-retaining patients.

Care should be exercised in administering solutions containing sodium or potassium to patients with renal or cardiovascular insufficiency, with or without congestive heart failure, particularly if they are postoperative or elderly.

Potassium therapy should be guided primarily by serial electrocardiograms, especially in patients receiving digitalis. Serum potassium levels are not necessarily indicative of tissue potassium levels.

Solutions containing calcium should be used with caution in the presence of cardiac disease, particularly when accompanied by renal disease. Parenteral calcium should be administered with extreme caution to patients receiving digitalis preparations.

Solutions containing lactate should be used with caution. Excess administration may result in metabolic alkalosis.

The conversion of lactate to bicarbonate is markedly delayed in the presence of tissue anoxia and reduced capacity of the liver to metabolize lactate. This may occur under conditions such as metabolic acidosis associated with circulatory insufficiency, extracorporeal circulation, hypothermia, glycogen storage disease, liver dysfunction, respiratory alkalosis, shock or cardiac decompensation.

To minimize the risk of possible incompatibilities arising from mixing this solution with other additives that may be prescribed, the final infusate should be inspected for cloudiness or precipitation immediately after mixing, prior to administration, and periodically during administration.

Do not use plastic container in series connection.

If administration is controlled by a pumping device, care must be taken to discontinue pumping action before the container runs dry or air embolism may result. If administration is not controlled by a pumping device, refrain from applying excessive pressure (>300mmHg) causing distortion to the container such as wringing or twisting. Such handling could result in breakage of the container.

This solution is intended for intravenous administration using sterile equipment. It is recommended that intravenous administration apparatus be replaced at least once every 24 hours.

Use only if solution is clear and container and seals are intact.

Laboratory Tests

Clinical evaluation and periodic laboratory determinations are necessary to monitor changes in fluid balance, electrolyte concentrations, and acid-base balance during prolonged parenteral therapy or whenever the condition of the patient warrants such evaluation. Significant deviations from normal concentrations may require tailoring of the electrolyte pattern, in this or an alternative solution.

Drug Interactions

Ceftriaxone

Precipitation of ceftriaxone-calcium can occur when ceftriaxone is mixed with calcium-containing solutions, such as Lactated Ringer’s Injection USP, in the same intravenous administration line. Do not administer ceftriaxone simultaneously with Lactated Ringer’s Injection USP via a Y-site. However, in patients other than neonates, ceftriaxone and Lactated Ringer’s Injection USP may be administered sequentially if the infusion lines are thoroughly flushed between infusions with a compatible fluid [see Warnings, Dosage and Administration].

Deaths have occurred in neonates (28 days of age or younger) who received concomitant intravenous calcium-containing solutions with ceftriaxone resulting from calcium-ceftriaxone precipitates in the lungs and kidneys, even when separate infusion lines were used [see Contraindications, Warnings, Pediatric Use, Dosage and Administration].

Some additives may be incompatible. Consult with pharmacist. When introducing additives, use aseptic techniques. Mix thoroughly. Do not store.

Carcinogenesis, Mutagenesis, Impairment of Fertility

Studies with Lactated Ringer's Injection USP have not been performed to evaluate carcinogenic potential, mutagenic potential, or effects on fertility.

Pregnancy: Teratogenic Effects

Animal reproduction studies have not been conducted with Lactated Ringer's Injection USP. It is also not known whether Lactated Ringer's Injection USP can cause fetal harm when administered to a pregnant woman or can affect reproduction capacity. Lactated Ringer's Injection USP should be given to a pregnant woman only if clearly needed.

Labor and Delivery

As reported in the literature, Lactated Ringer's Injection USP has been administered during labor and delivery. Caution should be exercised, and the fluid balance, glucose and electrolyte concentrations, and acid-base balance, of both mother and fetus should be evaluated periodically or whenever warranted by the condition of the patient or fetus.

Nursing Mothers

It is not known whether this drug is excreted in human milk. Because many drugs are excreted in human milk, caution should be exercised when Lactated Ringer's Injection USP is administered to a nursing woman.

Pediatric Use

Deaths have occurred in neonates (28 days of age or younger) who received concomitant intravenous calcium-containing solutions with ceftriaxone resulting from calcium-ceftriaxone precipitates in the lungs and kidneys, even when separate infusion lines were used. Lactated Ringer’s Injection USP is contraindicated in neonates receiving ceftriaxone [see Contraindications, Warnings, Drug Interactions].

Safety and effectiveness of Lactated Ringer's Injection USP in pediatric patients have not been established by adequate and well controlled trials, however, the use of electrolyte solutions in the pediatric population is referenced in the medical literature. The warnings, precautions, and adverse reactions identified in the label copy should be observed in the pediatric population.

Geriatric Use

Clinical studies of Lactated Ringer's Injection USP did not include sufficient numbers of subjects aged 65 and over to determine whether they respond differently from younger subjects. Other reported clinical experience has not identified differences in responses between the elderly and younger patients.

In general, dose selection for an elderly patient should be cautious, usually starting at the low end of the dosing range, reflecting the greater frequency of decreased hepatic, renal, or cardiac function, and of concomitant disease or other drug therapy.

ADVERSE REACTIONS

Allergic reactions or anaphylactoid symptoms such as localized or generalized urticaria and pruritus; periorbital, facial, and/or laryngeal edema; coughing, sneezing, and/or difficulty with breathing have been reported during administration of Lactated Ringer's Injection USP. The reporting frequency of these signs and symptoms is higher in women during pregnancy.

Reactions which may occur because of the solution or the technique of administration include febrile response, infection at the site of injection, venous thrombosis or phlebitis extending from the site of injection, extravasation and hypervolemia.

Symptoms may result from an excess or deficit of one or more of the ions present in the solution; therefore, frequent monitoring of electrolyte levels is essential.

Hypernatremia may be associated with edema and exacerbation of congestive heart failure due to the retention of water, resulting in an expanded extracellular fluid volume.

Reactions reported with the use of potassium-containing solutions include nausea, vomiting, abdominal pain and diarrhea. The signs and symptoms of potassium intoxication include paresthesias of the extremities, areflexia, muscular or respiratory paralysis, mental confusion, weakness, hypotension, cardiac arrhythmias, heart block, electrocardiographic abnormalities and cardiac arrest. Potassium deficits result in disruption of neuromuscular function, and intestinal ileus and dilatation.

If infused in large amounts, chloride ions may cause a loss of bicarbonate ions, resulting in an acidifying effect.

Abnormally high plasma levels of calcium can result in depression, amnesia, headaches, drowsiness, disorientation, syncope, hallucinations, hypotonia of both skeletal and smooth muscles, dysphagia, arrhythmias and coma. Calcium deficits can result in neuromuscular hyperexcitability, including cramps and convulsions.

Although the metabolism of lactate to bicarbonate is a relatively slow process, aggressive administration of sodium lactate may result in metabolic alkalosis. Careful monitoring of blood acid-base balance is essential during the administration of sodium lactate.

The physician should also be alert to the possibility of adverse reactions to drug additives. Prescribing information for drug additives to be administered in this manner should be consulted.

If an adverse reaction does occur, discontinue the infusion, evaluate the patient, institute appropriate therapeutic countermeasures and save the remainder of the fluid for examination if deemed necessary.

OVERDOSAGE

In the event of a fluid or solute overload during parenteral therapy, reevaluate the patient's condition and institute appropriate corrective treatment.

In the event of overdosage with potassium-containing solutions, discontinue the infusion immediately and institute corrective therapy to reduce serum potassium levels.

Treatment of hyperkalemia includes the following:

1. Dextrose Injection USP, 10% or 25%, containing 10 units of crystalline insulin per 20 grams of dextrose administered intravenously, 300 to 500 mL per hour.
2. Absorption and exchange of potassium using sodium or ammonium cycle cation exchange resin, orally and as retention enema.
3. Hemodialysis and peritoneal dialysis. The use of potassium-containing foods or medications must be eliminated. However, in cases of digitalization, too rapid a lowering of plasma potassium concentration can cause digitalis toxicity.

DOSAGE AND ADMINISTRATION

This solution is for intravenous use only.

Dosage is to be directed by a physician and is dependent upon age, weight, clinical condition of the patient and laboratory determinations. Frequent laboratory determinations and clinical evaluation are essential to monitor changes in blood glucose and electrolyte concentrations, and fluid and electrolyte balance during prolonged parenteral therapy.

Fluid administration should be based on calculated maintenance or replacement fluid requirements for each patient.

The presence of calcium ions in this solution should be considered when phosphate is present in additive solutions, in order to avoid precipitation.

Some additives may be incompatible. Consult with pharmacist. When introducing additives, use aseptic techniques. Mix thoroughly. Do not store.

Parenteral drug products should be inspected visually for particulate matter and discoloration prior to administration, whenever solution and container permit.

Ceftriaxone must not be administered simultaneously with calcium-containing intravenous solutions such as Lactated Ringer’s Injection USP via a Y-site. However, in patients other than neonates, ceftriaxone and Lactated Ringer’s Injection USP may be administered sequentially if the infusion lines are thoroughly are thoroughly flushed between infusions with a compatible fluid [see Contraindications, Warnings, Drug Interactions, Pediatric Use].

HOW SUPPLIED

Lactated Ringer's Injection USP is supplied sterile and nonpyrogenic in EXCEL® Containers. The 1000 mL containers are packaged 12 per case, the 500 mL and 250 mL containers are packaged 24 per case.

NDC | REF | Size
Lactated Ringer's Injection USP (Canada DIN 01931636)
76420-274-01; (relabeled from NDC; 0264-7750-00) | L7500 | 1000 mL

STORAGE AND HANDLING

Exposure of pharmaceutical products to heat should be minimized. Avoid excessive heat. Protect from freezing. It is recommended that the product be stored at room temperature (25°C); however, brief exposure up to 40°C does not adversely affect the product.

Revised: November 2021
EXCEL is a registered trademark of B. Braun Medical Inc.

Directions for Use of EXCEL Container

Caution: Do not use plastic container in series connection.

To Open

Tear overwrap down at notch and remove solution container. Check for minute leaks by squeezing solution container firmly. If leaks are found, discard solution as sterility may be impaired. If supplemental medication is desired, follow directions below before preparing for administration.

NOTE: Before use, perform the following checks:

- Inspect each container. Read the label. Ensure solution is the one ordered and is within the expiration date.
- Invert container and carefully inspect the solution in good light for cloudiness, haze, or particulate matter. Any container which is suspect should not be used.
- Use only if solution is clear and container and seals are intact.

Preparation for Administration

1. Remove plastic protector from sterile set port at bottom of container.
2. Attach administration set. Refer to complete directions accompanying set.

To Add Medication

Warning: Some additives may be incompatible.

To Add Medication Before Solution Administration

1. Prepare medication site.
2. Using syringe with 18–22 gauge needle, puncture medication port and inner diaphragm and inject.
3. Squeeze and tap ports while ports are upright and mix solution and medication thoroughly.

To Add Medication During Solution Administration

1. Close clamp on the set.
2. Prepare medication site.
3. Using syringe with 18–22 gauge needle of appropriate length (at least 5/8 inch), puncture resealable medication port and inner diaphragm and inject.
4. Remove container from IV pole and/or turn to an upright position.
5. Evacuate both ports by tapping and squeezing them while container is in the upright position.
6. Mix solution and medication thoroughly.
7. Return container to in use position and continue administration.

Relabeled by:

Enovachem PHARMACEUTICALS

Torrance, CA 90501